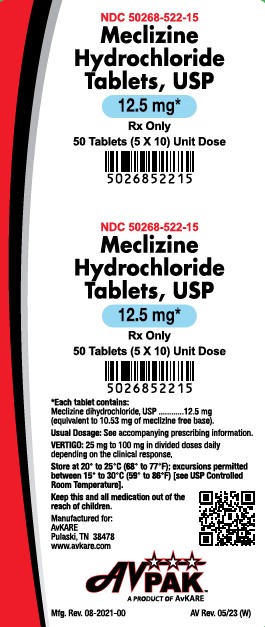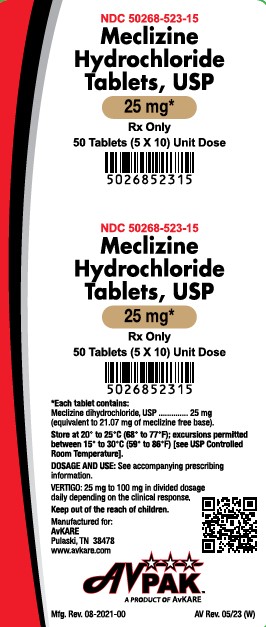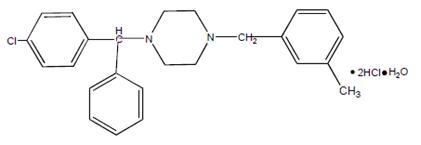 DRUG LABEL: Meclizine Hydrochloride
NDC: 50268-522 | Form: TABLET
Manufacturer: AvPAK
Category: prescription | Type: HUMAN PRESCRIPTION DRUG LABEL
Date: 20231026

ACTIVE INGREDIENTS: MECLIZINE HYDROCHLORIDE 12.5 mg/1 1
INACTIVE INGREDIENTS: SILICON DIOXIDE; LACTOSE MONOHYDRATE; MAGNESIUM STEARATE; CELLULOSE, MICROCRYSTALLINE; SODIUM STARCH GLYCOLATE TYPE A POTATO; TALC; FD&C BLUE NO. 1

Meclizine Hydrochloride Tablets, USP
Rx Only

DESCRIPTION

Chemically, meclizinehydrochloride, USP is 1-(p-chloro-α-phenylbenzyl)-4-(m-methylbenzyl) piperazine dihydrochloride monohydrate.

Inactive ingredients for the tablets are: colloidal silicon dioxide, lactose monohydrate, magnesium stearate, microcrystalline cellulose, sodium starch glycolate and talc. The 12.5 mg tablets also contain FD&C Blue #1 Aluminum Lake. The 25 mg tablets also contain D&C Yellow #10 Aluminum Lake.

CLINICAL PHARMACOLOGY

Meclizine hydrochloride is an antihistamine that shows marked protective activity against nebulized histamine and lethal doses of intravenously injected histamine in guinea pigs. It has a marked effect in blocking the vasodepressor response to histamine, but only a slight blocking action against acetylcholine. Its activity is relatively weak in inhibiting the spasmogenic action of histamine on isolated guinea pig ileum.

Pharmacokinetics

The available pharmacokinetic information for meclizine following oral administration has been summarized from published literature.

Absorption

Meclizine is absorbed after oral administration with maximum plasma concentrations reaching at a median Tmax value of 3 hours post-dose (range: 1.5 to 6 hours) for the tablet dosage form.

Distribution

Drug distribution characteristics for meclizine in humans are unknown.

Metabolism

The metabolic fate of meclizine in humans is unknown. In an in vitro metabolic study using human hepatic microsome and recombinant CYP enzyme, CYP2D6 was found to be the dominant enzyme for metabolism of meclizine.

The genetic polymorphism of CYP2D6 that results in extensive-, poor-, intermediate-and ultrarapid metabolizer phenotypes could contribute to large inter-individual variability in meclizine exposure.

Elimination

Meclizine has a plasma elimination half-life of about 5 to 6 hours in humans.

INDICATIONS AND USAGE

Meclizine hydrochloride tablets are indicated for the treatment of vertigo associated with diseases affecting the vestibular system.

CONTRAINDICATIONS

Meclizine hydrochloride is contraindicated in individuals who have shown a previous hypersensitivity to it.

WARNINGS

Since drowsiness may, on occasion, occur with use of this drug, patients should be warned of this possibility and cautioned against driving a car or operating dangerous machinery.

Patients should avoid alcoholic beverages while taking this drug.

Due to its potential anticholinergic action, this drug should be used with caution in patients with asthma, glaucoma, or enlargement of the prostate gland.

PRECAUTIONS

Pediatric Use

Clinical studies establishing safety and effectiveness in children have not been done; therefore, usage is not recommended in children under 12 years of age.

Pregnancy

Pregnancy Category B. Reproduction studies in rats have shown cleft palates at 25 to 50 times the human dose. Epidemiological studies in pregnant women, however, do not indicate that meclizine increases the risk of abnormalities when administered during pregnancy. Despite the animal findings, it would appear that the possibility of fetal harm is remote. Nevertheless, meclizine, or any other medication, should be used during pregnancy only if clearly necessary.

Nursing Mothers

It is not known whether this drug is excreted in human milk. Because many drugs are excreted in human milk, caution should be exercised when meclizine is administered to a nursing woman.

Hepatic Impairment

The effect of hepatic impairment on the pharmacokinetics of meclizine has not been evaluated. As meclizine undergoes metabolism, hepatic impairment may result in increased systemic exposure of the drug. Treatment with meclizine should be administered with caution in patients with hepatic impairment.

Renal Impairment The effect of renal impairment on the pharmacokinetics of meclizine has not been evaluated. Due to a potential for drug/metabolite accumulation, meclizine should be administered with caution in patients with renal impairment and in the elderly as renal function generally declines with age.

Drug Interactions

There may be increased CNS depression when meclizine is administered concurrently with other CNS depressants, including alcohol, tranquilizers and sedatives (see WARNINGS). Based on in vitro evaluation, meclizine is metabolized by CYP2D6. Therefore there is a possibility for a drug interaction between meclizine and CYP2D6 inhibitors.

ADVERSE REACTIONS

Anaphylactoid reaction, drowsiness, dry mouth, headache, fatigue, vomiting and, on rare occasions, blurred vision have been reported.

To report SUSPECTED ADVERSE REACTIONS, contact AvKARE at 1-855-361-3993; email drugsafety@avkare.com; or FDA at 1-800-FDA-1088 or www.fda.gov/medwatch.

DOSAGE AND ADMINISTRATION

For the treatment of vertigo associated with diseases affecting the vestibular system, the recommended dose is 25 mg to 100 mg daily, in divided dosage, depending upon clinical response.

HOW SUPPLIED

Meclizine Hydrochloride Tablets, USP 12.5 mg, are supplied as light blue colored, oval shaped tablets with “AN 441” debossed on one side and plain on the other side.

They are available as follows:
10 Tablets per card, 5 cards per carton: NDC 50268-522-15

Meclizine Hydrochloride Tablets, USP 25 mg, are supplied as light yellow colored, oval shaped tablets with “AN 442” debossed on one side and plain on the other side.
They are available as follows:
10 Tablets per card, 5 cards per carton: NDC 50268-523-15

Meclizine Hydrochloride Tablets, USP 50 mg, are supplied as white, oval shaped, partially bisected tablets with “AN 444” debossed on one side and plain on the other side.

Store at 20° to 25°C (68° to 77°F); excursions permitted between 15° to 30°C (59° to 86°F) [see USP Controlled Room Temperature].

Dispense in a tight, light-resistant container as defined in the USP.
Keep this and all medication out of the reach of children.

Manufactured for:
AvKARE
Pulaski, TN 38478

Mfg. Rev. 08-2021-00
AV Rev. 06/23 (M)
AvPAK